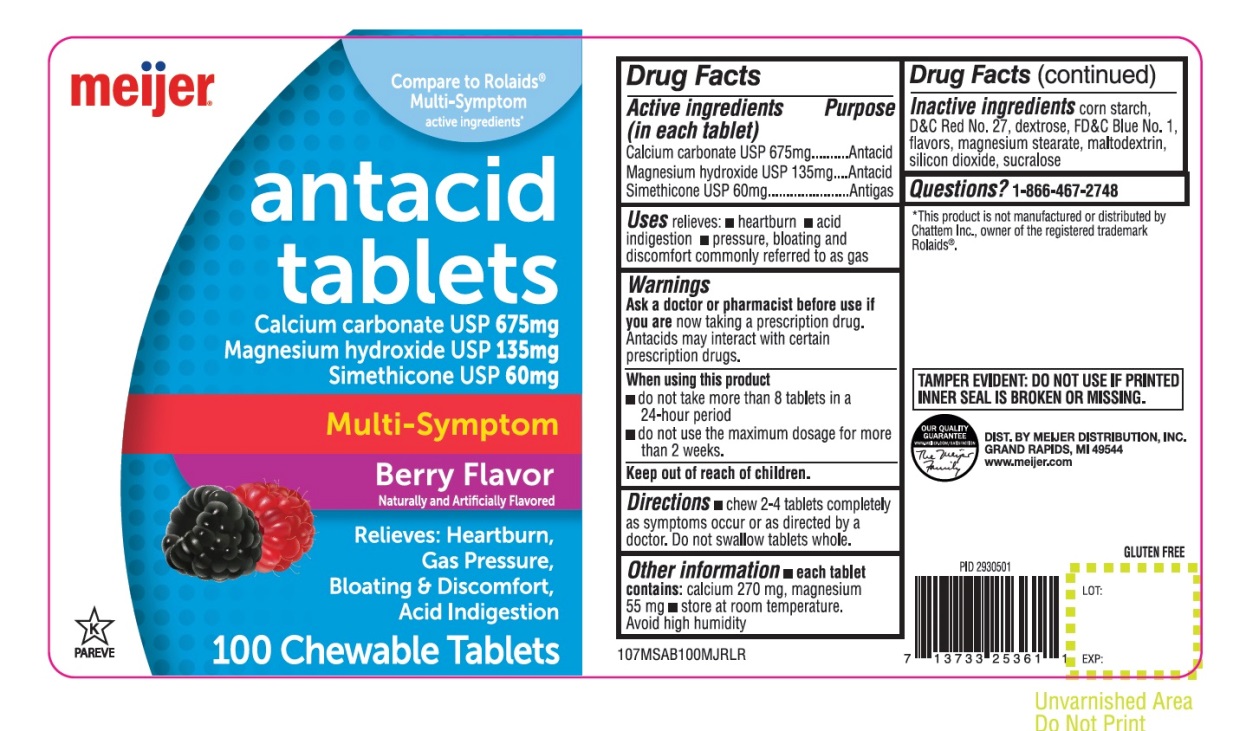 DRUG LABEL: Multi Symptom Antacid

NDC: 41250-427 | Form: TABLET, CHEWABLE
Manufacturer: MEIJER DISTRIBUTION, INC
Category: otc | Type: HUMAN OTC DRUG LABEL
Date: 20251024

ACTIVE INGREDIENTS: CALCIUM CARBONATE 675 mg/1 1; MAGNESIUM HYDROXIDE 135 mg/1 1; DIMETHICONE, UNSPECIFIED 60 mg/1 1
INACTIVE INGREDIENTS: STARCH, CORN; D&C RED NO. 27; DEXTROSE, UNSPECIFIED FORM; FD&C BLUE NO. 1; MAGNESIUM STEARATE; MALTODEXTRIN; SILICON DIOXIDE; SUCRALOSE

Meijer Multi Symptom 100 Chewable Tablets Berry Flavor

Drug Facts

Active ingredients(in each tablet)

Calcium Carbonate USP 675 mg
Magnesium hydroxide USP 135 mg

Simethicone USP 60mg

Purpose

Antacid

Antacid

Antigas

Uses

relieves:

- heartburn
- acid indigestion
- pressure, bloating and discomfort commonly referred to as gas

Warnings

Ask a doctor or pharmacist before use if you are

now taking a prescription drug. Antacids may interact with certain prescription drugs.

When using this product

- Do not take more than 8 tablets in a 24-hour period
- Do not use the maximum dosage for more than 2 weeks

Directions

- chew 2-4 tablets completely as symptoms occur or as directed by a doctor. Do not swallow tablets whole.

Other information

- each tablet contains:calcium 270 mg, magnesium 55 mg
- store at room temperature

Avoid high humidity

Inactive ingredients

corn starch, D&C Red No. 27, dextrose, FD&C Blue No. 1, flavor, magnesium stearate, maltodextrin, silicon dioxide, sucralose.

Questions?

1-866-467-2748

PRINCIPAL DISPLAY PANEL

NDC# 41250-427-10

*Compare To Rolaids®Multi-Symptom active ingredients

meijer®

Antacid Tablets

Calcium carbonate USP 675mg

Magnesium hydroxide USP 135mg

Simethicone USP 60 mg

Multi-Symptom

Berry Flavor

Naturally and Artificially Flavored

Relieves:

heartburn, gas pressure, bloating & discomfort, acid indigestion

GLUTEN FREE

K PAREVE

100 CHEWABLE TABLETS

OUR QUALITY GURANTEE

WWW.MEIJER.COM/SATISFACTION

*This product is not manufactured or distributed by Chattem Inc., owner of the registered trademark Rolaids®

TAMPER EVIDENT: DO NOT USE IF PRINTED INNER SEAL IS BROKEN OR MISSING.

DIST. BY: MEIJER DISTRIBUTION, INC.

GRAND RAPIDS, MI 49544

www.meijer.com